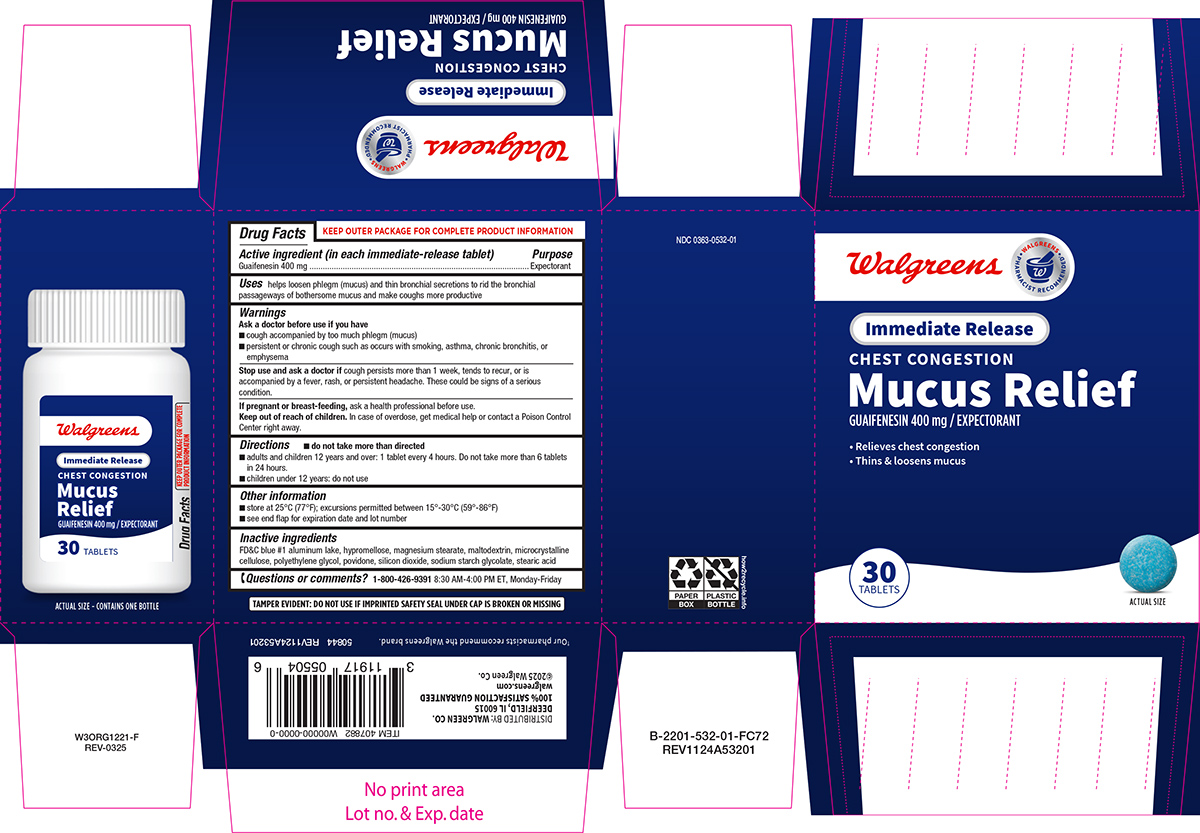 DRUG LABEL: Mucus Relief
NDC: 0363-0532 | Form: TABLET, FILM COATED
Manufacturer: Walgreen Company
Category: otc | Type: HUMAN OTC DRUG LABEL
Date: 20250411

ACTIVE INGREDIENTS: GUAIFENESIN 400 mg/1 1
INACTIVE INGREDIENTS: FD&C BLUE NO. 1 ALUMINUM LAKE; HYPROMELLOSE, UNSPECIFIED; MAGNESIUM STEARATE; MALTODEXTRIN; MICROCRYSTALLINE CELLULOSE; POLYETHYLENE GLYCOL, UNSPECIFIED; POVIDONE, UNSPECIFIED; SILICON DIOXIDE; SODIUM STARCH GLYCOLATE TYPE A POTATO; STEARIC ACID

Walgreens 44-532

Active ingredient (in each immediate-release tablet)

Guaifenesin 400 mg

Purpose

Expectorant

Uses

helps loosen phlegm (mucus) and thin bronchial secretions to rid the bronchial passageways of bothersome mucus and make coughs more productive

Warnings

Ask a doctor before use if you have

- cough accompanied by too much phlegm (mucus)
- persistent or chronic cough such as occurs with smoking, asthma, chronic bronchitis, or emphysema

Stop use and ask a doctor if

cough persists more than 1 week, tends to recur, or is accompanied by a fever, rash, or persistent headache. These could be signs of a serious condition.

If pregnant or breast-feeding,

ask a health professional before use.

Keep out of reach of children.

In case of overdose, get medical help or contact a Poison Control Center right away.

Directions

- do not take more than directed
- adults and children 12 years and over: 1 tablet every 4 hours. Do not take more than 6 tablets in 24 hours.
- children under 12 years: do not use

Other information

- store at 25ºC (77ºF); excursions permitted between 15º-30ºC (59º-86ºF)
- see end flap for expiration date and lot number

Inactive ingredients

FD&C blue #1 aluminum lake, hypromellose, magnesium stearate, maltodextrin, microcrystalline cellulose, polyethylene glycol, povidone, silicon dioxide, sodium starch glycolate, stearic acid

Questions or comments?

1-800-426-9391 8:30 AM-4:00 PM ET, Monday-Friday

Principal Display Panel

Walgreens

• WALGREENS •
PHARMACIST RECOMMENDED†

Immediate Release

CHEST CONGESTION
Mucus Relief

GUAIFENESIN 400 mg / EXPECTORANT

• Relieves chest congestion
• Thins & loosens mucus

30
TABLETS

ACTUAL SIZE

TAMPER EVIDENT: DO NOT USE IF IMPRINTED SAFETY SEAL UNDER CAP IS BROKEN OR MISSING

NDC 0363-0532-01

†Our pharmacists recommend the Walgreens brand.

50844 REV1124A53201

DISTRIBUTED BY: WALGREEN CO.
DEERFIELD, IL 60015
100% SATISFACTION GUARANTEED

walgreens.com
©2025 Walgreen Co.

ACTUAL SIZE - CONTAINS ONE BOTTLE

Walgreens 44-532